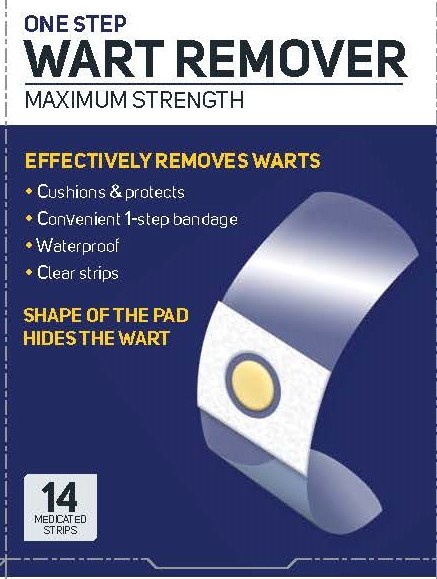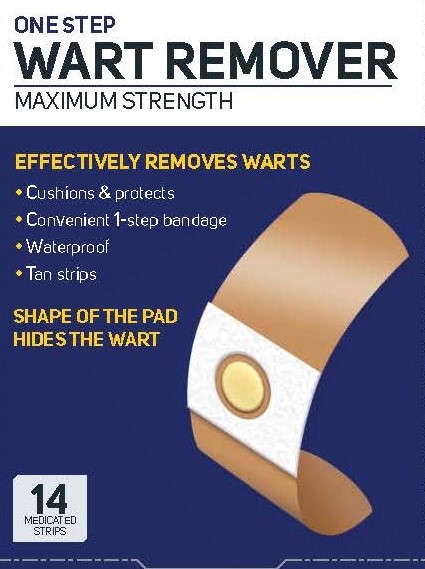 DRUG LABEL: Salicylic Acid Wart Remover
NDC: 51511-596 | Form: STRIP
Manufacturer: ASO Pharmaceutical Co. Ltd.
Category: otc | Type: HUMAN OTC DRUG LABEL
Date: 20251017

ACTIVE INGREDIENTS: SALICYLIC ACID 40 mg/1 1
INACTIVE INGREDIENTS: LANOLIN; NATURAL LATEX RUBBER

One Step Wart Remover Strips
Maximum Strength

Active ingredient

Salicylic acid 40%

Purpose

Wart remover

Uses

- for the removal of common warts. The common wart is easily recognized by the rough "cauliflower-like" appearance of the surface

Warnings

For External Use Only

Do not use

- on irritated skin or on any area that is infected or reddened
- on moles, birthmarks, warts with hair growing from them, genital warts, or on warts on the face or mucous membranes
- if you are diabetic
- if you have poor blood circulation

Stop use and ask a doctor if you have

discomfort persists

Keep out of reach of children.

In case of accidental ingestion, seek professional assistance or contact a Poison Control Center immediately.

Directions

- wash affected area
- may soak in warm water for 5 minutes
- dry area thoroughly
- remove medicated pad from backing paper by pulling from center of pad
- apply
- repeat procedure every 48 hours as needed until wart is removed for up to 12 weeks.

Other information

- store at room temperature
- avoid excessive heat 99ºF (37ºC)

Inactive ingredients

lanolin, polybutene, rosin ester, rubber

Distributed by:
ASO LLC
Sarasota, FL 34240

*This product is not manufactured or distributed by Medtech Products, Inc.,
owners of the registered trademark, Compound W®.

Principal Display Panel - Carton (Clear)

ONE STEP

WART REMOVER

MAXIMUM STRENGTH

EFFECTIVELY REMOVES WARTS

- Cushions & protects
- Convenient 1-step bandage
- Waterproof
- Clear strips

SHAPE OF THE PAD HIFES THE WART

Principal Display Panel - Carton (Tan)

ONE STEP

WART REMOVER

MAXIMUM STRENGTH

EFFECTIVELY REMOVES WARTS

- Cushions & protects
- Convenient 1-step bandage
- Waterproof
- Tan strips

SHAPE OF THE PAD HIFES THE WART